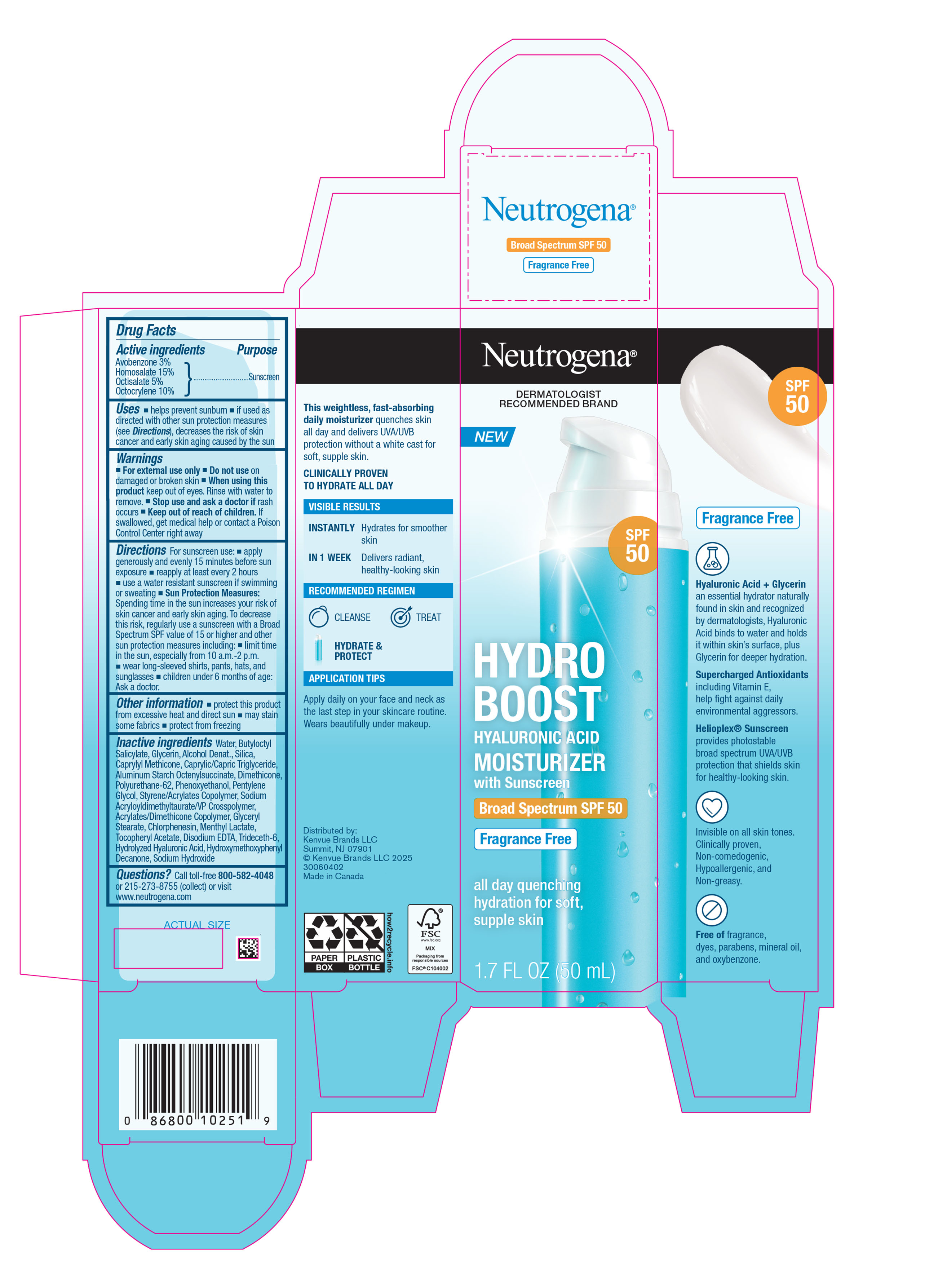 DRUG LABEL: Neutrogena Hydro Boost Hyaluronic Acid Moisturizer with Sunscreen Broad Spectrum SPF 50
NDC: 69968-0702 | Form: LOTION
Manufacturer: Kenvue Brands LLC
Category: otc | Type: HUMAN OTC DRUG LABEL
Date: 20251106

ACTIVE INGREDIENTS: AVOBENZONE 30 mg/1 mL; HOMOSALATE 150 mg/1 mL; OCTISALATE 50 mg/1 mL; OCTOCRYLENE 100 mg/1 mL
INACTIVE INGREDIENTS: HYALURONIC ACID; WATER; BUTYLOCTYL SALICYLATE; GLYCERIN; ALCOHOL; SILICON DIOXIDE; CAPRYLYL TRISILOXANE; MEDIUM-CHAIN TRIGLYCERIDES; ALUMINUM STARCH OCTENYLSUCCINATE; DIMETHICONE; POLYURETHANE-62	; PHENOXYETHANOL; PENTYLENE GLYCOL; BUTYL METHACRYLATE/METHYL METHACRYLATE/METHACRYLIC ACID/STYRENE CROSSPOLYMER; GLYCERYL MONOSTEARATE; CHLORPHENESIN; MENTHYL LACTATE, (-)-; .ALPHA.-TOCOPHEROL ACETATE; EDETATE DISODIUM ANHYDROUS; TRIDECETH-6; 1-(4-HYDROXY-3-METHOXYPHENYL)-DECAN-3-ONE; SODIUM HYDROXIDE

Neutrogena® HYDRO BOOST HYALURONIC ACID MOISTURIZER with Sunscreen Broad Spectrum SPF 50

Drug Facts

ACTIVE INGREDIENT

Active ingredients | Purpose
Avobenzone 3% | Sunscreen
Homosalate 15% | Sunscreen
Octisalate 5% | Sunscreen
Octocrylene 10%. | Sunscreen

Uses

- helps prevent sunburn
- if used as directed with other sun protection measures (see Directions), decreases the risk of skin cancer and early skin aging caused by the sun

Warnings

For external use only

Do not use on damaged or broken skin

When using this product keep out of eyes. Rinse with water to remove.

Stop use and ask a doctor if rash occurs

Keep out of reach of children. If swallowed, get medical help or contact a Poison Control Center right away

Directions

For sunscreen use:

- apply generously and evenly 15 minutes before sun exposure
- reapply at least every 2 hours
- use a water resistant sunscreen if swimming or sweating
- Sun Protection Measures: Spending time in the sun increases your risk of skin cancer and early skin aging. To decrease this risk, regularly use a sunscreen with a Broad Spectrum SPF value of 15 or higher and other sun protection measures including:
  - limit time in the sun, especially from 10 a.m.-2 p.m.
  - wear long-sleeved shirts, pants, hats, and sunglasses
- children under 6 months of age: Ask a doctor.

Other information

- protect this product from excessive heat and direct sun
- may stain some fabrics
- protect from freezing

Inactive ingredients

Water, Butyloctyl Salicylate, Glycerin, Alcohol Denat., Silica, Caprylyl Methicone, Caprylic/Capric Triglyceride, Aluminum Starch Octenylsuccinate, Dimethicone, Polyurethane-62, Phenoxyethanol, Pentylene Glycol, Styrene/Acrylates Copolymer, Sodium Acryloyldimethyltaurate/VP Crosspolymer, Acrylates/Dimethicone Copolymer, Glyceryl Stearate, Chlorphenesin, Menthyl Lactate, Tocopheryl Acetate, Disodium EDTA, Trideceth-6, Hydrolyzed Hyaluronic Acid, Hydroxymethoxyphenyl Decanone, Sodium Hydroxide

Questions?

Call toll-free 800-582-4048 or 215-273-8755 (collect) or visit www.neutrogena.com

Distributed by:
Kenvue Brands LLC
Summit, NJ 07901

PRINCIPAL DISPLAY PANEL - 50 mL Bottle Carton

Neutrogena®
DERMATOLOGIST
RECOMMENDED BRAND

New

SPF
50

HYDRO
BOOST
HYALURONIC ACID
MOISTURIZER
with Sunscreen
Broad Spectrum SPF 50
Fragrance Free

all day quenching
hydration for soft,
supple skin

1.7 FL OZ (50mL)